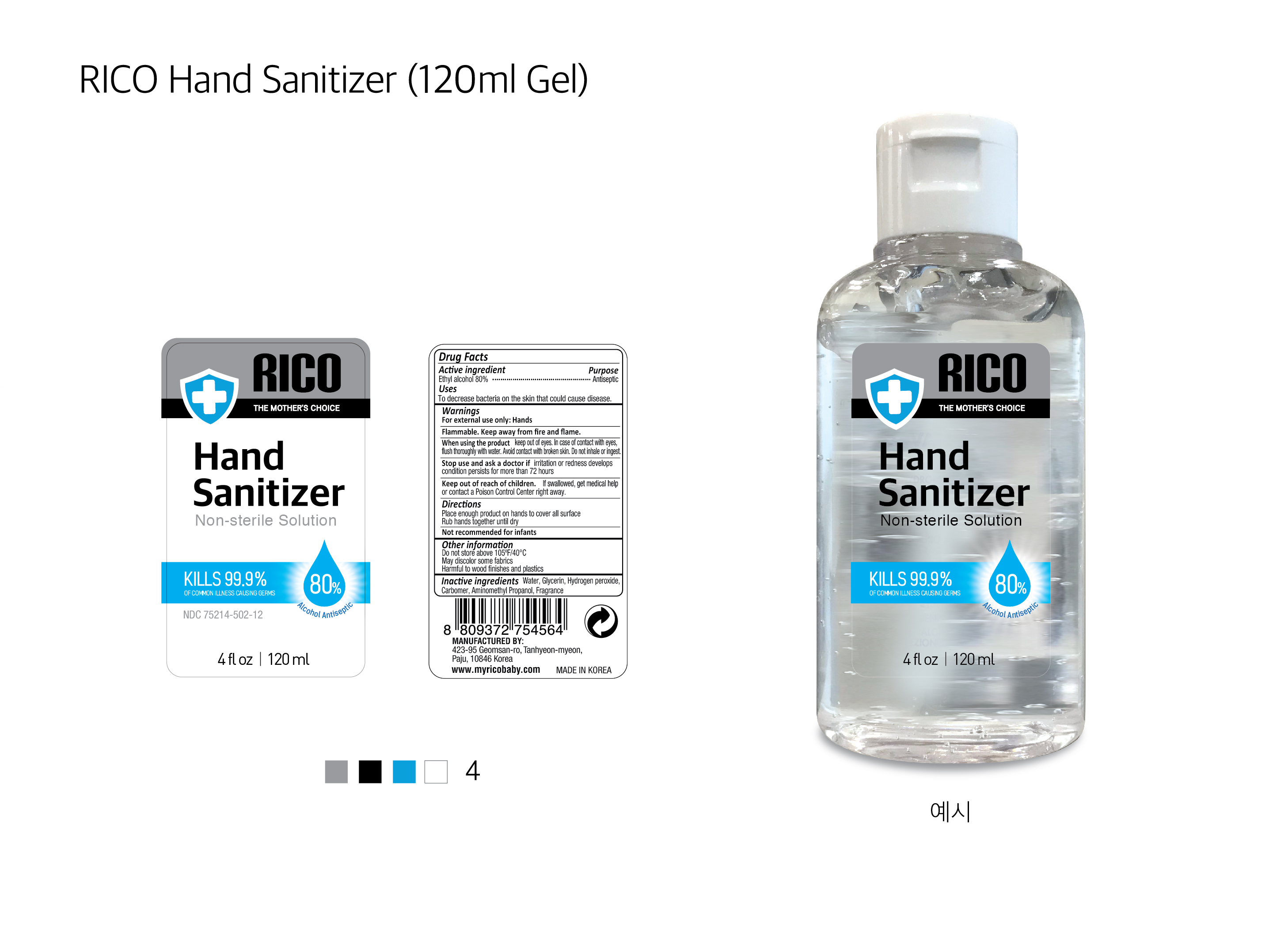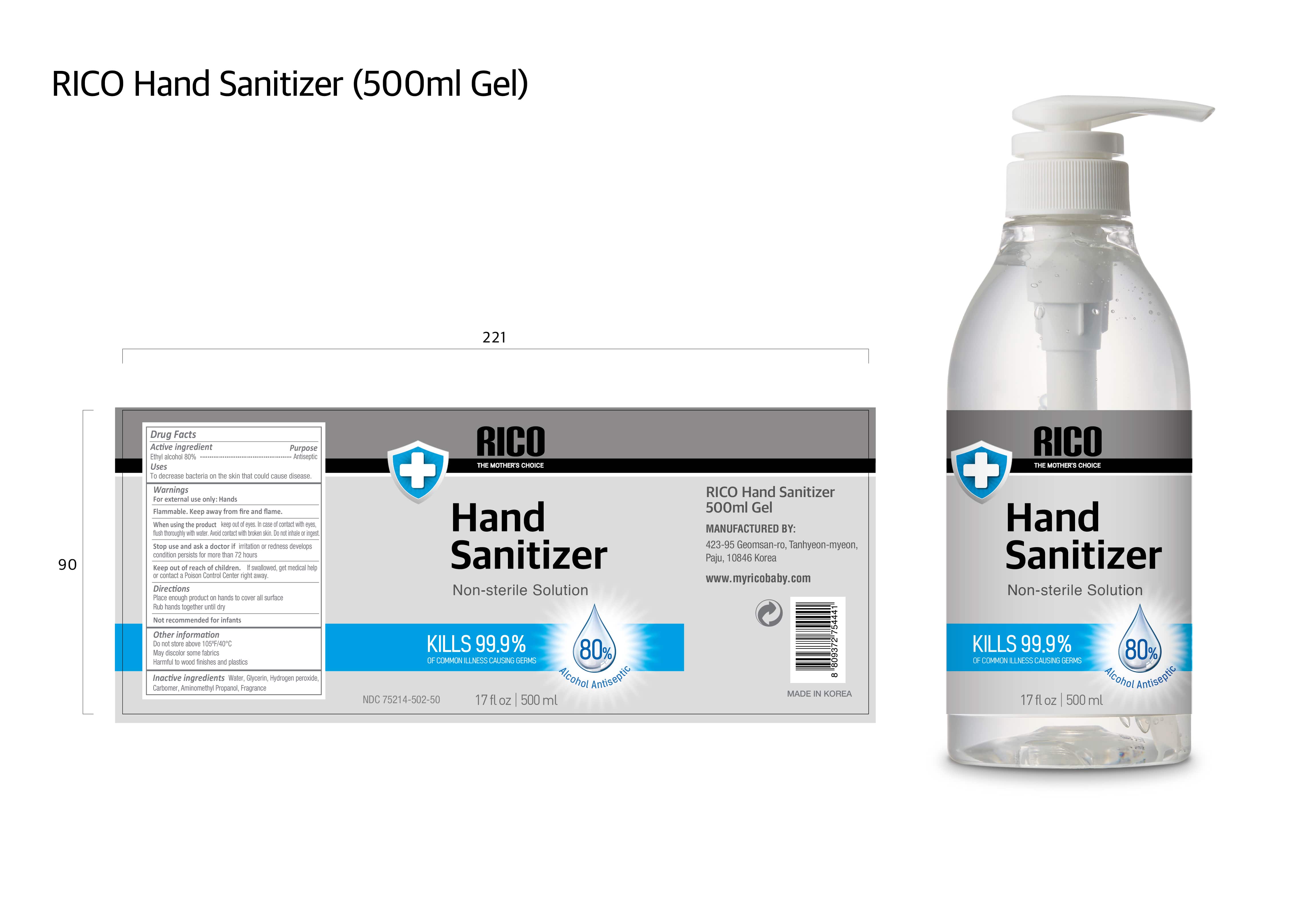 DRUG LABEL: Hand Sanitizer
NDC: 75214-502 | Form: LIQUID
Manufacturer: HANUL CO.,LTD
Category: otc | Type: HUMAN OTC DRUG LABEL
Date: 20250120

ACTIVE INGREDIENTS: ALCOHOL 80 mL/100 mL
INACTIVE INGREDIENTS: GLYCERIN 1.45 mL/100 mL; HYDROGEN PEROXIDE 0.12 mL/100 mL; WATER 17.68 mL/100 mL; CARBOMER HOMOPOLYMER TYPE C (ALLYL PENTAERYTHRITOL CROSSLINKED) 0.4 mL/100 mL; AMINOMETHYLPROPANOL 0.3 mL/100 mL

hand sanitizer gel Rico 500ml and 120ml

Active Ingredient(s)

Alcohol 80% v/v. Purpose: Antiseptic

Purpose

Antiseptic, Hand Sanitizer

Use

to decrease bacteria on the skin that can cause disease.

Warnings

For external use only: hands. Flammable. Keep away from fire or flame

WHEN USING

When using the product keep out of eyes. In case of contact with eyes flush thoroughly with water. Avoid contact with broken skin. Do not inhale or ingest.

Stop use and ask a doctor if irritation or redness develops condition persists for more than 72 hours

Keep out of reach of children. If swallowed, get medical help or contact a Poison Control Center right away.

Directions

Place enough product to hands to cover all surface

Rub hands together until dry

Not recommended for infants

Other information

do not store above105°F/40°C

May discolor some fabrics

Harmful to wood finishes and plastics

Inactive ingredients

Water. Glycerin, Hydrogen peroxide, Carbomer, Aminomethyl Propanol, Fragrance

Package Label - Principal Display Panel

500 mL NDC: 75214-502-50

120mL NDC: 75214-502-12